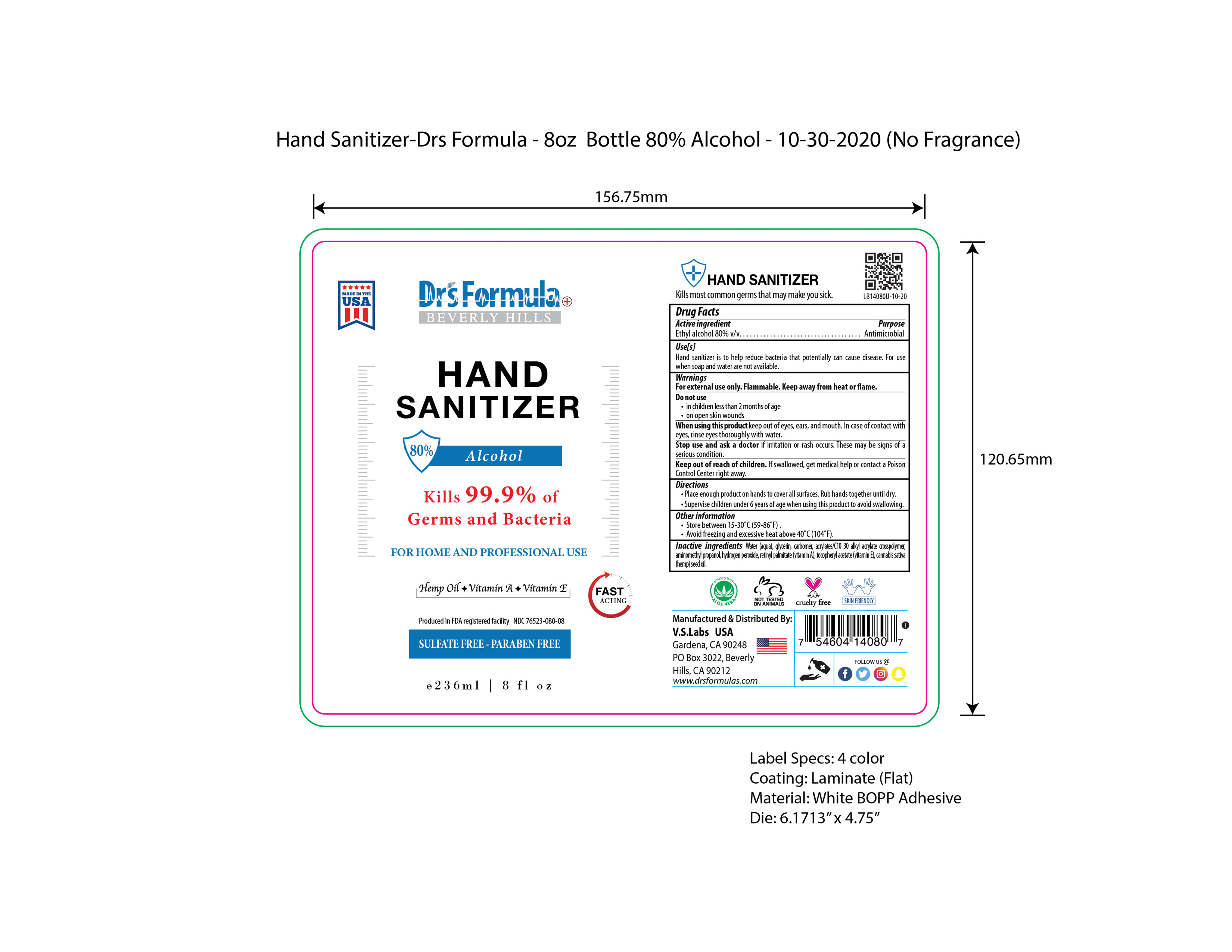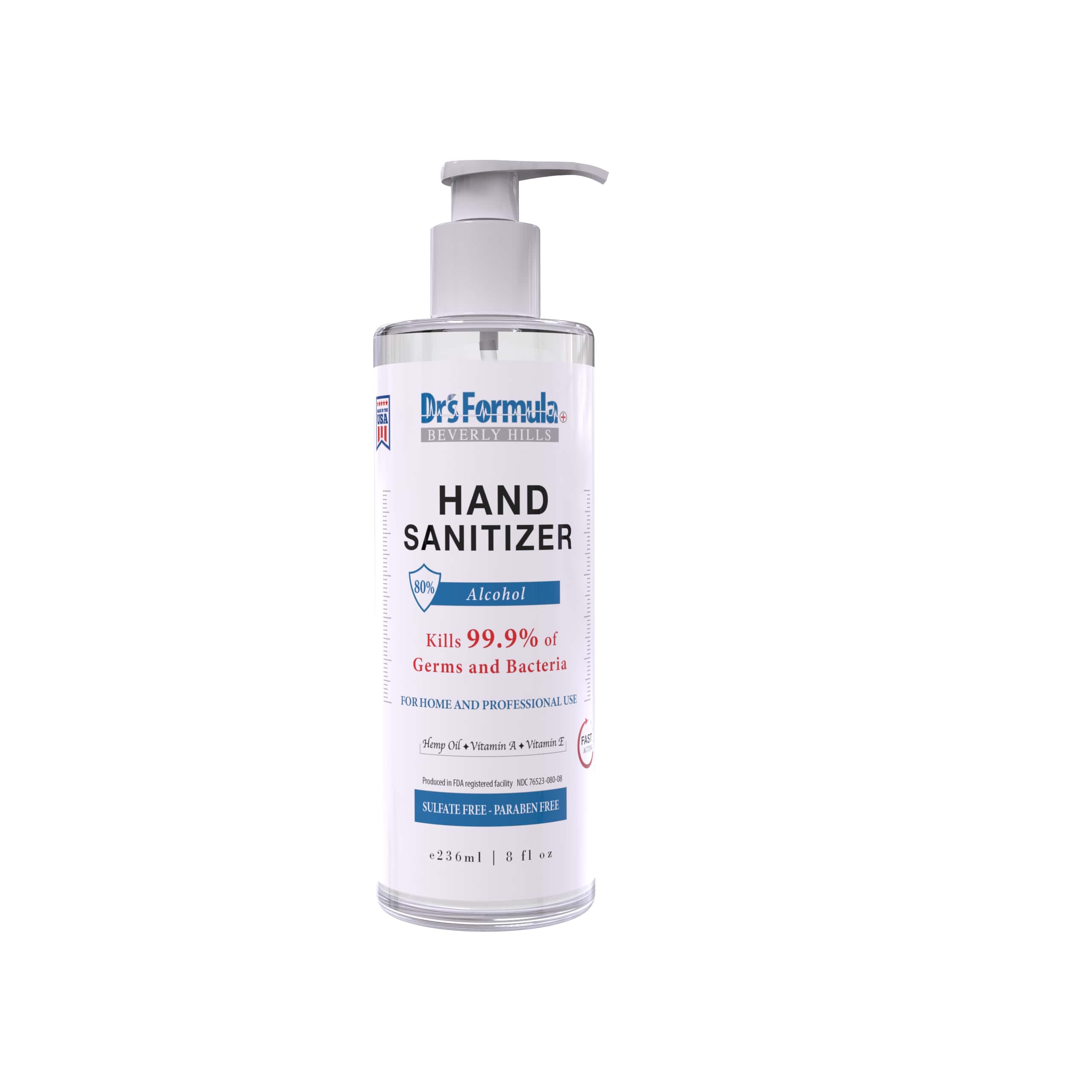 DRUG LABEL: Hand Sanitizer
NDC: 76523-080 | Form: GEL
Manufacturer: Valley of the Sun Cosmetics LLC
Category: otc | Type: HUMAN OTC DRUG LABEL
Date: 20201116

ACTIVE INGREDIENTS: ALCOHOL 80 mL/100 mL
INACTIVE INGREDIENTS: ALPHA-TOCOPHEROL ACETATE 0.05 mL/100 mL; AMINOMETHYLPROPANOL 0.06 mL/100 mL; (C10-C30)ALKYL METHACRYLATE ESTER 0.2 mL/100 mL; HYDROGEN PEROXIDE 0.125 mL/100 mL; VITAMIN A PALMITATE 0.03 mL/100 mL; CARBOMER 934 0.01 mL/100 mL; WATER 18.05 mL/100 mL; GLYCERIN 1.45 mL/100 mL; CANNABIS SATIVA SEED OIL 0.02 mL/100 mL

Hand Sanitizer (no fragrance)

Active Ingredients

Ethyl Alcohol 80% v/v

Purpose

Antimicrobial

Uses

Hand Sanitizer is to help reduce bacteria that potentially can cause disease. For use when soap and water are not available.

Warnings

For external use only. Flammable. Keep away from heat or flame.

Do not use

- in children less than 2 months of age
- on open skin wounds

When using this product

keep out of eyes, ears, and mouth. In case of contact with eyes, rinse eyes thoroughly with water.

Stop use and ask doctor if irritation or rash occurs. These may be signs of a serious condition.

Keep out of reach of children

If swallowed, get medical help or contact a Poison Control Center right away.

Directions

- Place enough product on hands to cover all surfaces. Rub hands together until dry.
- Supervise children under 6 years of age when using this product to avoid swallowing.

Other information

- Store between 15-30ºC (59-86°F)
- Avoid freezing and excessive heat above 40ºC (104°F)

Inactive Ingredients

Water (aqua), glycerin, carbomer, acrylates/C10 30 alkyl acrylate crosspolymer, aminomethyl propanol, hydrogen peroxide, retinyl palmitate (vitamin A), tocopheryl acetate (vitamin E), cannabis sativa (hemp) seed oil

Package Label

Hand Sanitizer 80% Alcohol (no fragrance), 8oz/236ml, NDC: 76523-080-08